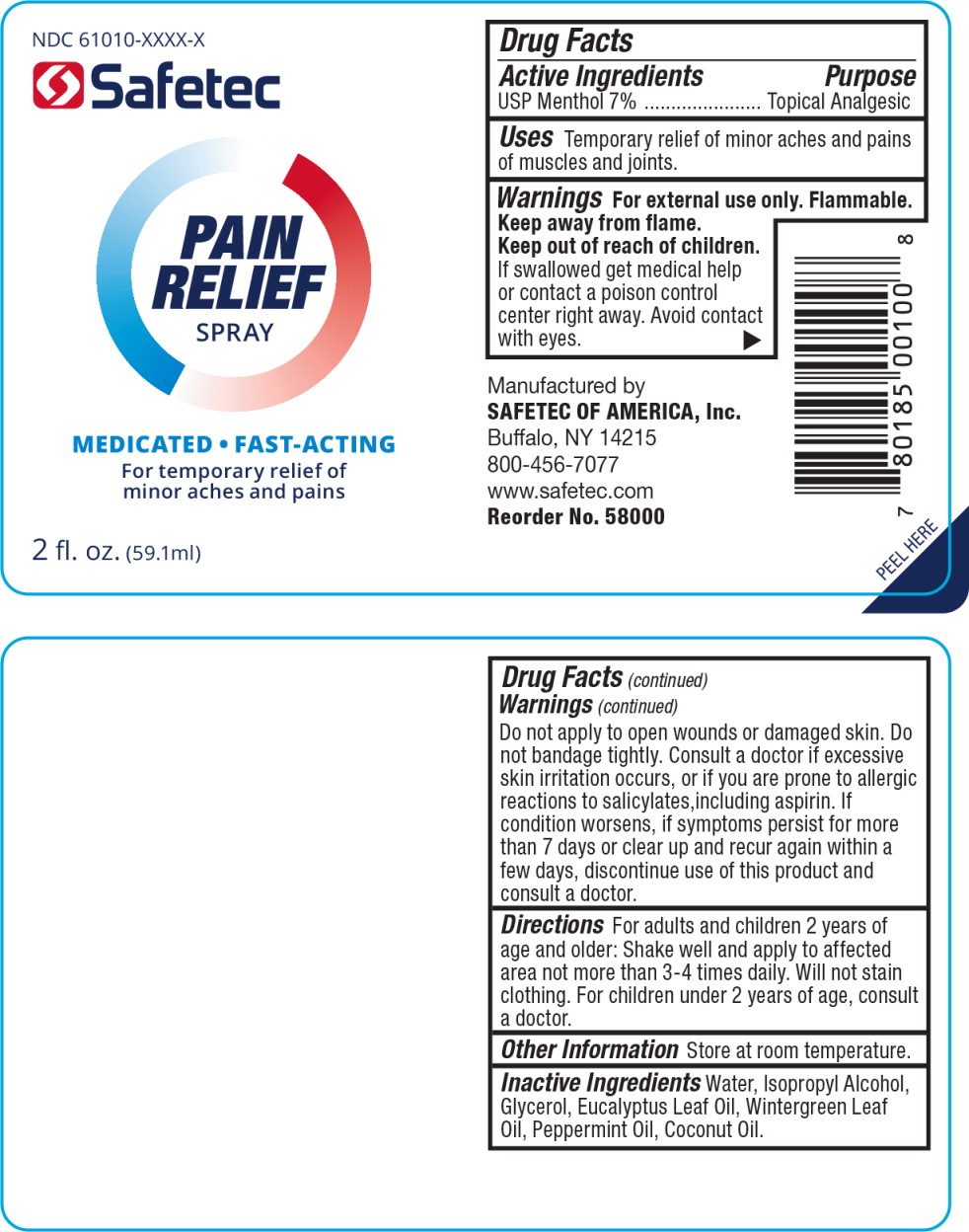 DRUG LABEL: Analgesic
NDC: 61010-8201 | Form: SPRAY
Manufacturer: Safetec of America, Inc.
Category: otc | Type: HUMAN OTC DRUG LABEL
Date: 20240204

ACTIVE INGREDIENTS: MENTHOL 70 mg/1 L
INACTIVE INGREDIENTS: WATER; ISOPROPYL ALCOHOL; GLYCERIN; EUCALYPTUS OIL; METHYL SALICYLATE; PEPPERMINT OIL; COCONUT OIL

61010-8201. Pain Relief Spray

Active Ingredients

USP Menthol 7%

Purpose

Topical Analgesic

Uses

Temporary relief of minor aches and pains of muscles and joints.

Warnings

For external use only.

Flammable.

Keep away from flame.

Keep out of reach of children.

If swallowed get medical help or contact a poison control center right away. Avoid contact with eyes.

DO NOT USE

Do not apply to open wounds or damaged skin. Do not bandage tightly.

ASK DOCTOR

Consult a doctor if excessive skin irritation occurs, or if you are prone to allergic reactions to salicylates,including aspirin. If condition worsens, if symptoms persist for more than 7 days or clear up and recur again within a few days, discontinue use of this product and consult a doctor.

Directions

For adults and children 2 years of age and older: Shake well and apply to affected area not more than 3-4 times daily. Will not stain clothing. For children under 2 years of age, consult a doctor.

Other Information

Store at room temperature.

Inactive Ingredients

Water, Isopropyl Alcohol, Glycerol, Eucalyptus Leaf Oil, Wintergreen Leaf Oil, Peppermint Oil, Coconut Oil.

Principal Display Panel - Pain Relief Spray Bottle Label

NDC 61010-XXXX-X

Safetec

PAIN
RELIEF
SPRAY

MEDICATED FAST-ACTING

For temporary relief of minor aches and pains

2 fl. oz. (59.1 ml)